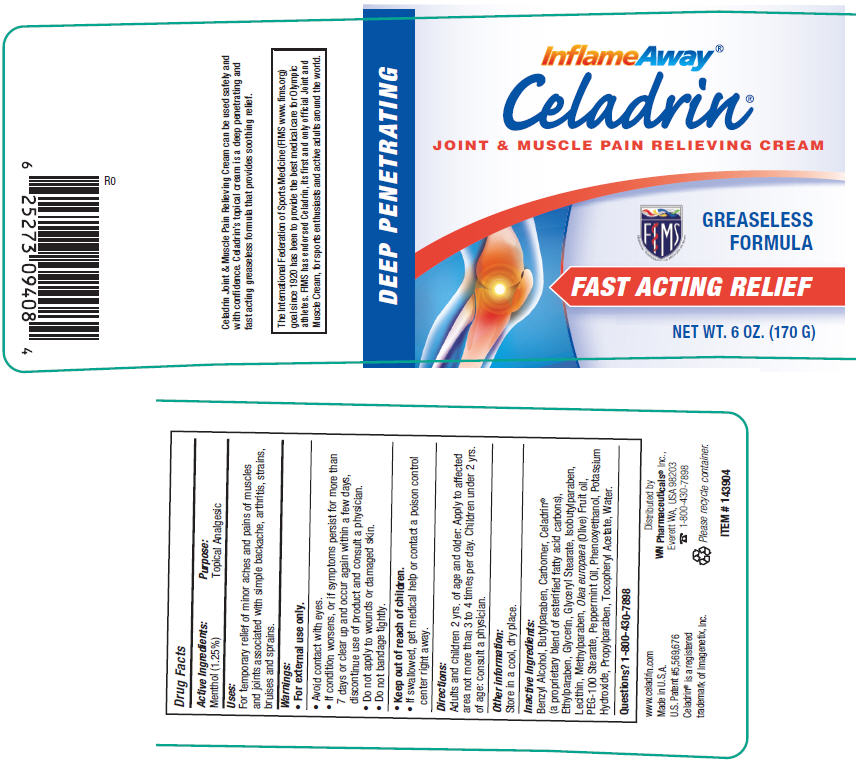 DRUG LABEL: Celadrin
NDC: 54230-356 | Form: CREAM
Manufacturer: Factors Group of Nutritional Products
Category: otc | Type: HUMAN OTC DRUG LABEL
Date: 20231106

ACTIVE INGREDIENTS: MENTHOL 12.5 mg/1 g
INACTIVE INGREDIENTS: BENZYL ALCOHOL; BUTYLPARABEN; CARBOMER INTERPOLYMER TYPE A (ALLYL SUCROSE CROSSLINKED); ETHYLPARABEN; GLYCERIN; GLYCERYL MONOSTEARATE; ISOBUTYLPARABEN; LECITHIN, SOYBEAN; METHYLPARABEN; OLIVE OIL; PEG-100 STEARATE; PEPPERMINT OIL; PHENOXYETHANOL; SODIUM HYDROXIDE; PROPYLPARABEN; .ALPHA.-TOCOPHEROL ACETATE; WATER

Factors Group (as PLD) - Celadrin Joint and Muscle Pain Relieving Cream (54230-356)

Drug Facts

Active Ingredients

Menthol (1.25%)

Purpose

Topical Analgesic

Uses

For temporary relief of minor aches and pains of muscles and joints associated with simple backache, arthritis, strains, bruises and sprains.

Warnings

- For external use only.

WHEN USING

- Avoid contact with eyes.
- If condition worsens, or if symptoms persist for more than 7 days or clear up and occur again within a few days, discontinue use of product and consult a physician.
- Do not apply to wounds or damaged skin.
- Do not bandage tightly.

- Keep out of reach of children.
- If swallowed, get medical help or contact a poison control center right away.

Directions

Adults and children 2 yrs. of age and older: Apply to affected area not more than 3 to 4 times per day. Children under 2 yrs. of age: consult a physician.

Other information

Store in a cool, dry place.

Inactive Ingredients

Benzyl Alcohol, Butylparaben, Carbomer, Celadrin®(a proprietary blend of esterified fatty acid carbons), Ethylparaben, Glycerin, Glyceryl Stearate, Isobutylparaben, Lecithin, Methylparaben, Olea europaea(Olive) Fruit oil, PEG-100 Stearate, Peppermint Oil, Phenoxyethanol, Potassium Hydroxide, Propylparaben, Tocopheryl Acetate, Water.

Questions?

1-800-430-7898

Distributed by
WN Pharmaceuticals®Inc.,
Everett WA, USA 98203

PRINCIPAL DISPLAY PANEL - 170 g Jar Label

DEEP PENETRATING

InflameAway®

Celadrin®

JOINT & MUSCLE PAIN RELIEVING CREAM

FIMS

GREASELESS
FORMULA

FAST ACTING RELIEF

NET WT. 6 OZ. (170 G)